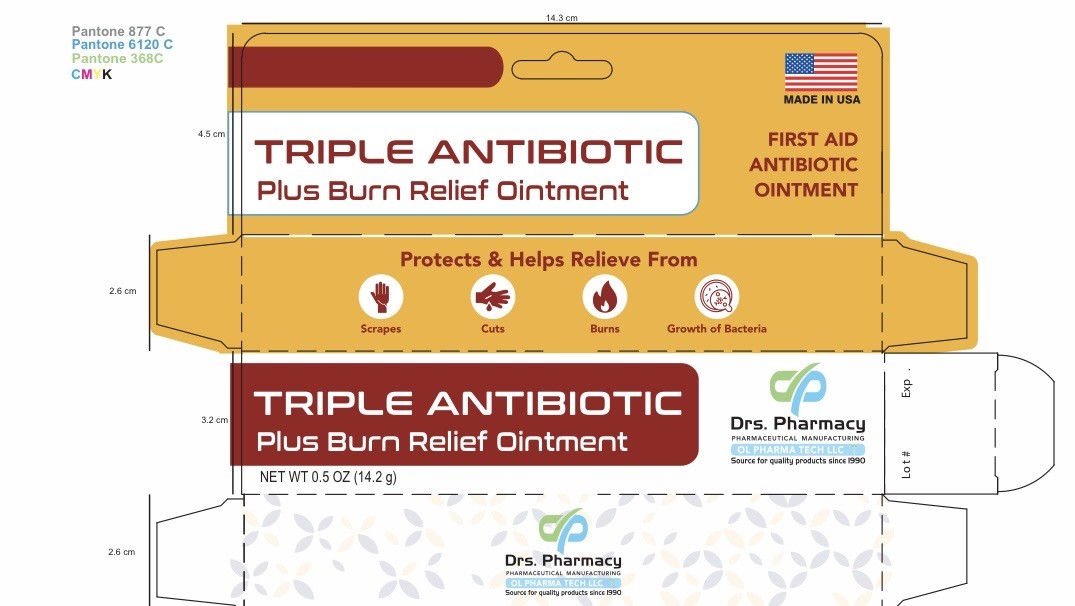 DRUG LABEL: Drs. Pharmacy Triple Antibiotic AND BURN RELIEF
NDC: 80489-919 | Form: OINTMENT
Manufacturer: OL PHARMA TECH, LLC Drs PHARMACY
Category: otc | Type: HUMAN OTC DRUG LABEL
Date: 20260122

ACTIVE INGREDIENTS: BACITRACIN ZINC 500 [USP'U]/1000 mg; NEOMYCIN SULFATE 3.5 mg/1000 mg; POLYMYXIN B SULFATE 10000 [USP'U]/1000 mg; PRAMOXINE HYDROCHLORIDE 10 mg/1000 mg
INACTIVE INGREDIENTS: PETROLATUM

Active ingredients

Bacitracin zinc 500 units
Neomycin 3.5 mg
Polymyxin B sulfate 10,000 units

Pramoxine hydrochloride 10 mg

Uses

first aid to help prevent infection in minor
• cuts
• scrapes
• burns

Purpose

- first aid antibiotic
- External Analgesic

Do Not Use

• if you are allergic to any of the ingredients
• in the eyes
• over large areas of the body
• longer than 1 week unless directed by a doctor

WARNINGS

For external use only

Ask a doctor before use if you have
• deep or puncture wounds
• animal bites
• serious burns

Stop use and ask a doctor if
• the condition persists or gets worse
• a rash or other allergic reaction develops

KEEP OUT OF REACH OF CHILDREN

If swallowed, get medical help or contact a Poison Control Center right away.

DIRECTIONS

• clean the affected area
• apply a small amount of this product (an amount equal to the surface area of the tip of a finger) on the area 1 to 3 times daily
• may be covered with a sterile bandage

OTHER INFORMATION

Store at room temperature

Inactive Ingredient

Petrolatum

QUESTIONS

www.drspharmacyusa.com